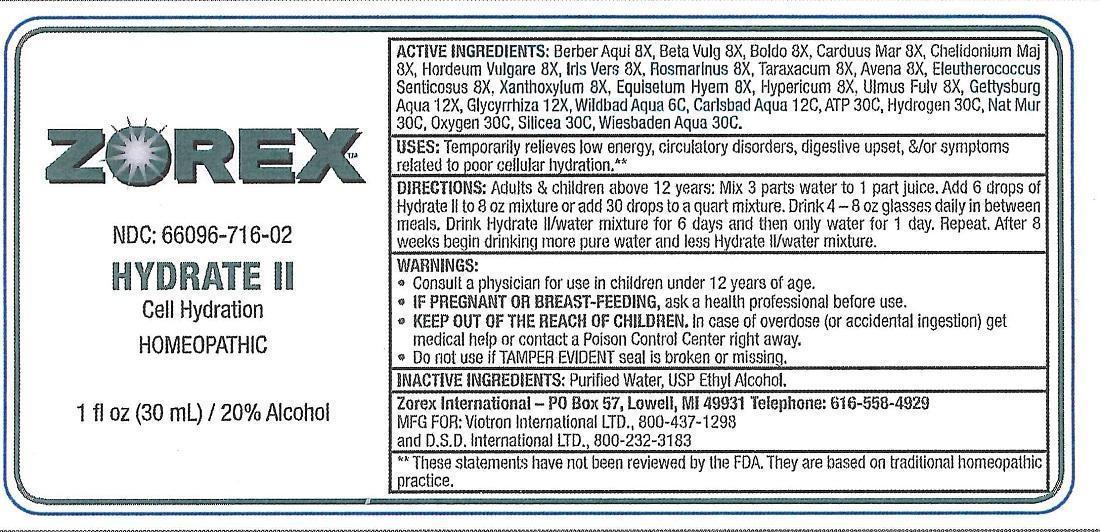 DRUG LABEL: Hydrate II
NDC: 66096-716 | Form: LIQUID
Manufacturer: OHM PHARMA INC.
Category: homeopathic | Type: HUMAN OTC DRUG LABEL
Date: 20170314

ACTIVE INGREDIENTS: BERBERIS AQUIFOLIUM ROOT BARK 8 [hp_X]/30 mL; BETA VULGARIS 8 [hp_X]/30 mL; PEUMUS BOLDUS LEAF 8 [hp_X]/30 mL; MILK THISTLE 8 [hp_X]/30 mL; CHELIDONIUM MAJUS 8 [hp_X]/30 mL; BARLEY 8 [hp_X]/30 mL; IRIS VERSICOLOR ROOT 8 [hp_X]/30 mL; ROSMARINUS OFFICINALIS FLOWERING TOP 8 [hp_X]/30 mL; TARAXACUM OFFICINALE 8 [hp_X]/30 mL; AVENA SATIVA FLOWERING TOP 8 [hp_X]/30 mL; ELEUTHERO 8 [hp_X]/30 mL; ZANTHOXYLUM AMERICANUM BARK 8 [hp_X]/30 mL; EQUISETUM HYEMALE 8 [hp_X]/30 mL; HYPERICUM PERFORATUM 8 [hp_X]/30 mL; ULMUS RUBRA BARK 8 [hp_X]/30 mL; GLYCYRRHIZA GLABRA 12 [hp_X]/30 mL; ADENOSINE TRIPHOSPHATE 30 [hp_C]/30 mL; HYDROGEN 30 [hp_C]/30 mL; SODIUM CHLORIDE 30 [hp_C]/30 mL; OXYGEN 30 [hp_C]/30 mL; SILICON DIOXIDE 30 [hp_C]/30 mL
INACTIVE INGREDIENTS: ALCOHOL; WATER

Hydrate II

ACTIVE INGREDIENT

ACTIVE INGREDIENTS: Berber Aqui 8X, Beta Vulg 8X, Boldo 8X, Carduus Mar 8X, Chelidonium Maj 8X, Hordeum Vulgare 8X, Iris Vers 8X, Rosmarinus 8X, Taraxacum 8X, Avena 8X, Eleutherococcus Senticosus 8X, Xanthoxylum 8X, Equisetum Hyem 8X, Hypericum 8X, Ulmus Fulv 8X, Gettysburg Aqua 12X, Glycyrrhiza 12X, Wildbad Aqua 6C, Carlsbad Aqua 12C, ATP 30C, Hydrogen 30C, Nat Mur 30C, Oxygen 30C, Silicea 30C, Wiesbaden Aqua 30C.

INDICATIONS AND USAGE

USES: Temporarily relieves low energy, circulatory disorders, digestive upset, &/or symptoms related to poor cellular hydration.**

**These statements have not been reviewed by the FDA. They are based on traditional homeopathic practice.

DOSAGE AND ADMINISTRATION

DIRECTIONS: Adults & children above 12 years: Mix 3 parts water to 1 part juice. Add 6 drops of Hydrate II to 8 oz mixture or add 30 drops to a quart mixture. Drink 4 - 8 oz glasses daily in between meals. Drink Hydrate II/water mixture for 6 days and then only water for 1 day. Repeat. After 8 weeks begin drinking more pure water and less Hydrate II/water mixture.

WARNINGS:

- Consult a physician for use in children under 12 years of age.
- IF PREGNANT OR BREAST-FEEDING, ask a health professional before use.
- KEEP OUT OF THE REACH OF CHILDREN. In case of overdose (or accidental ingestion) get medical help or contact a Poison Control Center right away.
- Do not use if TAMPER EVIDENT seal is broken or missing.

Keep out of reach of children.

INACTIVE INGREDIENTS: Purified Water, USP Ethyl Alcohol.

QUESTIONS

Zorex International - PO Box 57, Lowell, MI 49931 Telephone: 616-558-4929

MFG FOR: Viotron International LTD., 800-437-1298

and D.S.D. International LTD., 800-232-3183

PURPOSE

Cell Hydration

PACKAGE LABEL

ZOREX

NDC: 66096-716-02

HYDRATE II

Cell Hydration

HOMEOPATHIC

1 fl oz (30 mL) / 20% Alcohol